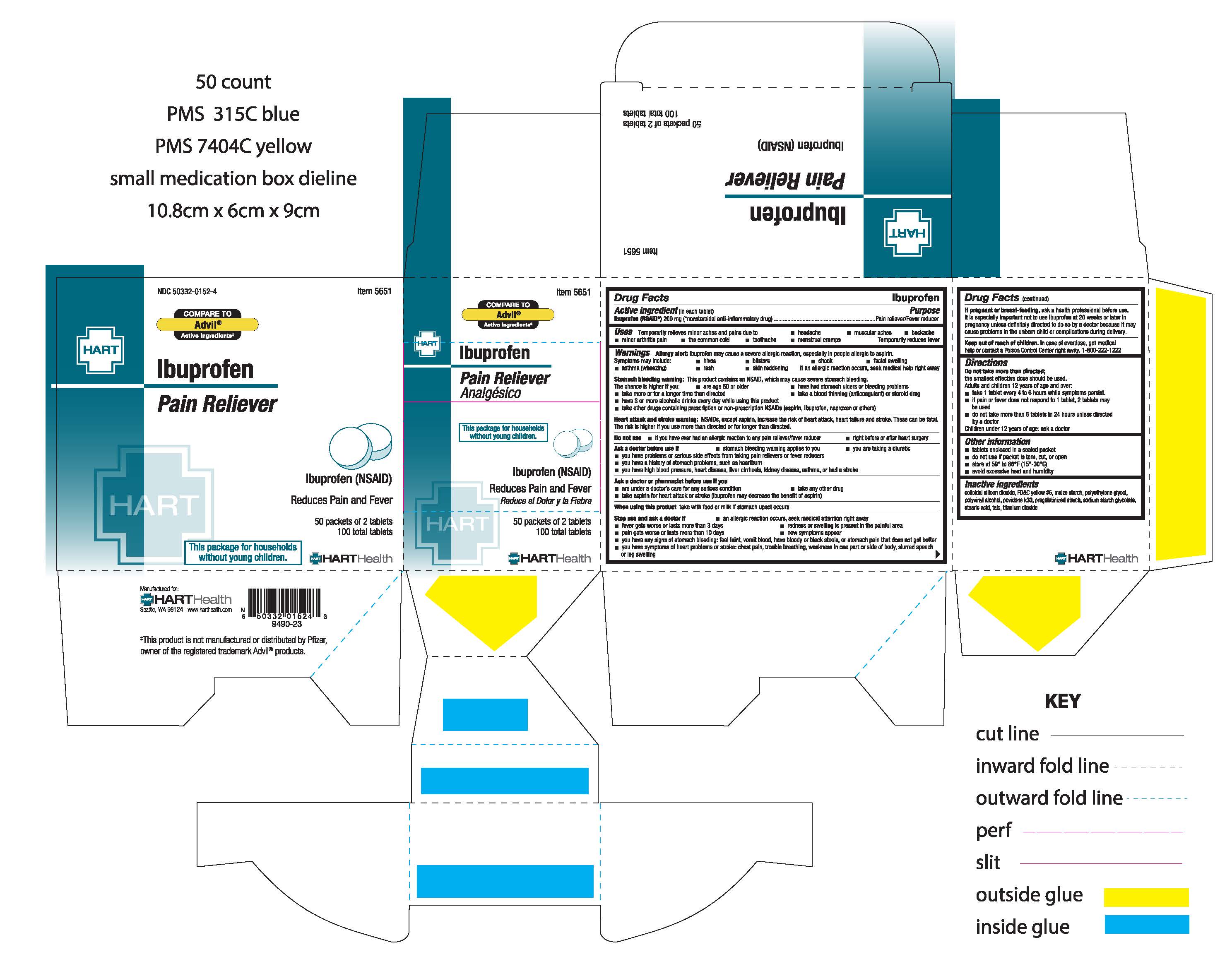 DRUG LABEL: IBUPROFEN
NDC: 50332-0152 | Form: TABLET
Manufacturer: HART Health
Category: otc | Type: HUMAN OTC DRUG LABEL
Date: 20240125

ACTIVE INGREDIENTS: IBUPROFEN 200 mg/1 1
INACTIVE INGREDIENTS: CROSCARMELLOSE SODIUM; MAGNESIUM STEARATE; CELLULOSE, MICROCRYSTALLINE; SILICON DIOXIDE; TITANIUM DIOXIDE; STARCH, CORN; POLYVINYL ALCOHOL, UNSPECIFIED; TALC; TRIACETIN; HYPROMELLOSES; POLYETHYLENE GLYCOL, UNSPECIFIED

IBUPROFEN

Active Ingredient (in each tablet): Ibuprofen (NSAID*) 200mg (*nonsteroidal anti-inflammatory drug)

Purpose: Pain Reliever / Fever Reducer

INDICATIONS AND USAGE

Uses: Temporarily relieves minor aches and pains due to

- headache
- muscular aches
- backache
- minor arthritis pain
- the common pain
- toothache
- menstrual cramps

Temporarily reduces fever

Warnings:

Allergy alert: Ibuprofen may cause a severe allergic reaction, especially in people allergic to aspirin. Symptoms may include:

- hives
- rash
- shock
- facial swelling
- asthma (wheezing)
- skin reddening
- blisters

Stomach bleeding warning: This product contains an NSAID, which may cause stomach bleeding. The chance is higher if you:

- are age 60 or older
- have had stomach ulcers or bleeding problems
- take more or for a longer time than directed
- take a blood thinning (anticoagulant) or steroid drug
- have 3 or more alcoholic drinks every day while using this product
- take other drugs containing prescription or non-prescriptin NSAIDs (aspirin, ibuprofen, naproxen, or others)

Do not use

- if you have ever had an allergic reaction to any other pain reliever/fever reducer
- right before or after heart surgery

Ask a doctor before use if

- stomach bleeding warning applies to you
- you have a history of stomach problems, such as heartburn
- you have high blood pressure, heart disease, liver cirrhosis, or kidney disease
- you are taking a diuretic

Ask a doctor or pharmacist before use if you

- take any other drug containing an NSAID
- take a blood thinning (anticoagulant) or steroid drug
- take aspirin for heart attach or stroke (ibuprofen may decrease the benefit if aspirin)
- are under a doctor's care for any serious condition

When using this product

- take with food or milk if stomach upset occurs
- long term continuous use may increase the risk of heart attack or stroke

Stop use and ask a doctor if

- an allergic reaction occurs, seek medical help right away
- fever gets worse or lasts more than 3 days
- pain gets worse or lasts more than 10 days
- redness or swelling is present in the painful area
- new symptoms occur
- you have any of the following signs of stomach bleeding: feel faint, vomit blood, have bloody or black stools, or stomach pain that does not get better

PREGNANCY OR BREAST FEEDING

If pregnant or breast-feeding, ask a health professional before use. It is especially important not to use ibuprofen during the last 3 months of pregnancy unless definitely directed to do so by a doctor because it may cause problems in the unborn child or complications during delivery

Keep out of reach of children. In case of overdose, get medical help or contact a Poison Control Center right away. 1-800-222-1222

Directions:

Do not take more than directed; the smallest effective dose should be used.

Adults and children 12 years of age and over:

- take 1 tablet every 4 to 6 hours while symptoms persist
- if pain or fever does not respond to 1 tabet, 2 tablets may be used
- do not take more than 6 tablets in 24 hours unless directed by a doctor

Children under 12 years of age: ask a doctor

INACTIVE INGREDIENT

Inactive Ingredients: Colloidal Silicon Dioxide, Corn Starch*, Croscarmellose Sodium*, Hypromellose*, Magnesium Stearate, Microcrystalline Cellulose, Polyethylene Glycol*, Polyvinyl Alcohol*, Pregelantinized Starch, Red Iron Oxide, Sodium Starch Glycolate*, Talc, Titanium Dioxide, Triacetin*.

*Contains one or more of these ingredients.